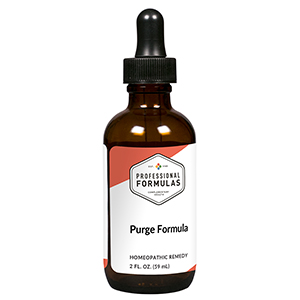 DRUG LABEL: Purge Formula
NDC: 63083-2066 | Form: LIQUID
Manufacturer: Professional Complementary Health Formulas
Category: homeopathic | Type: HUMAN OTC DRUG LABEL
Date: 20190815

ACTIVE INGREDIENTS: MELIA AZEDARACH WHOLE 3 [hp_X]/59 mL; COMBRETUM INDICUM WHOLE 3 [hp_X]/59 mL; CUCURBITA PEPO SUBSP. OVIFERA WHOLE 3 [hp_X]/59 mL; TORREYA NUCIFERA SEED OIL 3 [hp_X]/59 mL; HONEY MUSHROOM 3 [hp_X]/59 mL
INACTIVE INGREDIENTS: ALCOHOL; WATER

C66

ACTIVE INGREDIENTS

Melia 3X, 6X, 12X, 30X
Quisqualis 3X, 6X, 12X, 30X
Cucurbita pepo 3X, 6X, 12X, 30X
Torreya 3X, 6X, 12X, 30X
Omphalia 3X, 6X, 12X, 30X

QUESTIONS

Professional Formulas

PO Box 2034 Lake Oswego, OR 97035

INDICATIONS

For the temporary relief of minor abdominal pain or cramps, gas or bloating, feeling tired, or periodic nausea.*

PURPOSE

*Claims based on traditional homeopathic practice, not accepted medical evidence. Not FDA evaluated.

WARNINGS

Severe or persistent symptoms may be a sign of a serious condition. Consult a doctor promptly if symptoms persist or are accompanied by a fever, vomiting, diarrhea, or loss of appetite. Keep out of the reach of children. In case of overdose, get medical help or contact a poison control center right away. If pregnant or breastfeeding, ask a healthcare professional before use.

Keep out of the reach of children.

PREGNANCY OR BREAST FEEDING

If pregnant or breastfeeding, ask a healthcare professional before use.

DIRECTIONS

Place drops under tongue 30 minutes before/after meals. Adults and children 12 years and over: Take 10 drops up to 3 times per day. Consult a physician for use in children under 12 years of age.

OTHER INFORMATION

Tamper resistant. If seal is broken, do not use. After opening, close container tightly and store at room temperature away from heat.

INACTIVE INGREDIENTS

20% ethanol, purified water.

LABEL

Est 1985

Professional Formulas

Complementary Health

Purge Formula

Homeopathic Remedy

2 FL. OZ. (59 mL)